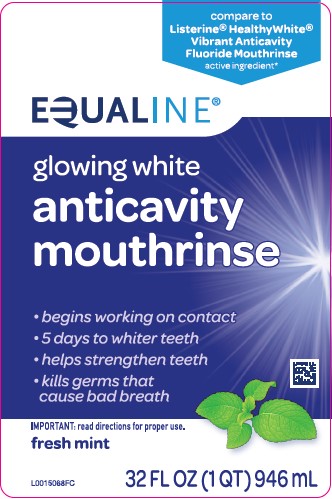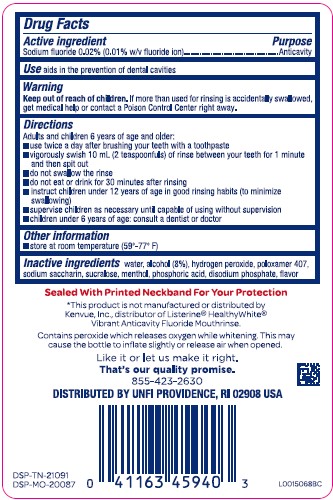 DRUG LABEL: Anticavity
NDC: 41163-011 | Form: MOUTHWASH
Manufacturer: United Natural Foods, Inc. dba UNFI
Category: otc | Type: HUMAN OTC DRUG LABEL
Date: 20260217

ACTIVE INGREDIENTS: SODIUM FLUORIDE 0.1 mg/1 mL
INACTIVE INGREDIENTS: ALCOHOL; HYDROGEN PEROXIDE; POLOXAMER 407; SACCHARIN SODIUM; WATER; SUCRALOSE; MENTHOL; PHOSPHORIC ACID; SODIUM PHOSPHATE, DIBASIC, ANHYDROUS

Equaline 435.000/435AA
Glowing White Anticavity Mouthrinse

Active Ingredient

Sodium fluoride 0.02% (0.01% w/v fluoride ion)

Purpose

Anticavity

Use

Aids in the prevention of dental cavities

Warnings

For this product

Keep out of reach of children.

If more than used for rinsing is accidentally swallowed, get medical help or contact a Poison Control Center right away.

Directions

Adults and children 6 years of age and older:

- use twice a day after brushing your teeth with a toothpaste
- vigorously swish 10 mL (2 teaspoonfuls) of rinse between your teeth for 1 minute and then spit out
- do not swallow the rinse
- do not eat or drink for 30 minutes after rinsing
- instruct children under 12 years of age in good rinsing habits (to minimize swallowing)
- supervise children as necessary until capable of using without supervision
- children under 6 years of age: consult a dentist or doctor

Other information

Store at room temperature (59º-77ºF)

Inactive ingredients

water, alcohol (8%), hydrogen peroxide, poloxamer 407, sodium saccharin, sucralose, menthol, phosphoric acid, disodium phosphate, flavor

TEP

Sealed With Printed Neckband For Your Protection

Disclaimer

*This product is not manufactured or distributed by Kenvue, Inc., distributor of Listerine® HealthyWhite® Vibrant Anticavity Fluoride Mouthrinse.

Other information

Contains peroxide which releases oxgen while whitening. This may cause the bottle to inflate slightly or release air when opened.

Adverse reactions section

Like it or let us make it right.

That's out quality promise.

855-423-2630

DISTRIBUTED BY UNFI PROVIDENCE, RI 02908 USA

DSP-TN-210091

DSP-MO-20087

Principal display panel

compare to Listerine® HealthyWhite® Vibrant Anticavity Fluoride Mouthrinse active ingredient*

EQUALINE®

glowing white

anticavity

mouthrinse

- begins working on contact
- 5 days to whiter teeth
- helps strengthen teeth
- kills germs that cause bad breath

IMPORTANT: read directions for proper use.

fresh mint

32 FL OZ (1 QT) 946 mL